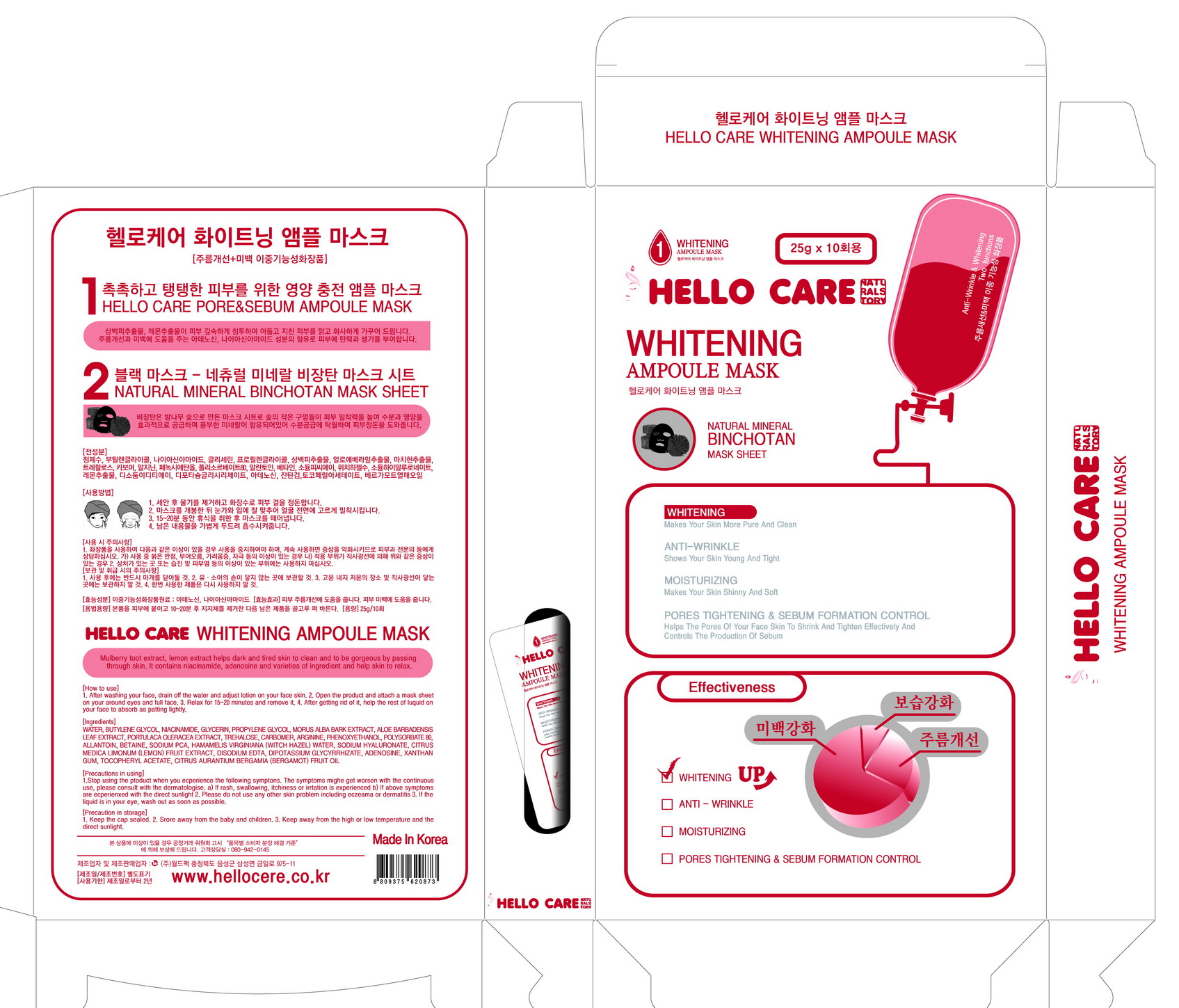 DRUG LABEL: HELLO CARE WHITENING AMPOULE MASK
NDC: 70959-0003 | Form: PATCH
Manufacturer: WORLD PACK CO., LTD.
Category: otc | Type: HUMAN OTC DRUG LABEL
Date: 20160917

ACTIVE INGREDIENTS: ADENOSINE 0.04 g/100 g; NIACINAMIDE 2 g/100 g
INACTIVE INGREDIENTS: WATER; BUTYLENE GLYCOL

Drug Facts

ACTIVE INGREDIENT

ADENOSINE, NIACINAMIDE

INACTIVE INGREDIENT

WATER, BUTYLENE GLYCOL, ETC.

PURPOSE

- Skin Protectant
- Whitening

keep out of reach of the children

INDICATIONS AND USAGE

1. After washing your face, drain off the water and adjust lotion on your face skin.
2. Open the product and attach a mask sheet on your aroun eyes and full face.
3. Relax for 15~20 minutes and remove it.
4. After getting rid of it, help the rest of liquid on your fact to absorb as patting lightly.

WARNINGS

1. Do not use in the following cases(Eczema and scalp wounds)

2.Side Effects

1)Due to the use of this product, if rash, irritation, itching and symptopms of hypersnesitivity occur dicontinue use and consult your pharmacist or doctor

3.General Precautions

1)If in contact with the eyes, wash out thoroughty with water If the symptoms are servere, seek medical advice immediately

2)This product is for exeternal use only. Do not use for internal use

4.Storage and handling precautions

1)If possible, avoid direct sunlight and store in cool and area of low humidity

2)In order to maintain the quality of the product and avoid misuse

3)Avoid placing the product near fire and store out in reach of children

DOSAGE AND ADMINISTRATION

for external use only